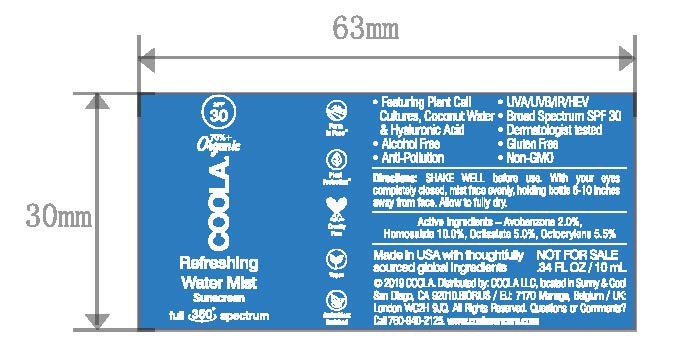 DRUG LABEL: COOLA Refreshing Water Mist Sunscreen
NDC: 21839-590 | Form: LIQUID
Manufacturer: Gordon Laboratories, Inc.
Category: otc | Type: HUMAN OTC DRUG LABEL
Date: 20191226

ACTIVE INGREDIENTS: AVOBENZONE 20 mg/1 mL; HOMOSALATE 100 mg/1 mL; OCTISALATE 50 mg/1 mL; OCTOCRYLENE 55 mg/1 mL
INACTIVE INGREDIENTS: ETHYL OLIVATE; CETYL PALMITATE; POLYOXYL 20 CETOSTEARYL ETHER; TROPOLONE; LAURYL GLUCOSIDE; GLYCERYL STEARATE SE; CAPRYLYL GLYCOL; CETEARYL ISONONANOATE; COCONUT WATER; CETEARETH-12; BUTYLENE GLYCOL; PHYTATE SODIUM; PROPANEDIOL; JASMINUM SAMBAC FLOWER; MEDIUM-CHAIN TRIGLYCERIDES; BENZOIC ACID; ALCOHOL; 1,2-HEXANEDIOL; COCOA; SODIUM STEAROYL GLUTAMATE; GLYCERIN; CETOSTEARYL ALCOHOL; ALOE VERA LEAF; SOYBEAN; WATER; HYALURONATE SODIUM; SCHINUS MOLLE FRUITING TOP

COOLA Refreshing Water Mist Sunscreen SPF 30

ACTIVE INGREDIENT

Active Ingredients - Avobenzone 2.0%, Homosalate 10.0%, Octisalate 5.0%, Octocrylene 5.5%

Questions or comments? Call 760-940-2125

INDICATIONS AND USAGE

Directions: SHAKE WELL before use. With your eyes completely closed, mist face evenly, holding bottle 6-10 inces away from face. Allow to fully dry.

DESCRIPTION

* Featuring Plant Cell Cultures, Coconut Water & hyaluronic Acid

* Alcohol Free

* Anti-Pollution

* UVA/UVB/IR/HEV

* Broad Spectrum SPF 30

* Dermatologist tested

* Gluten Free

* Non-GMO